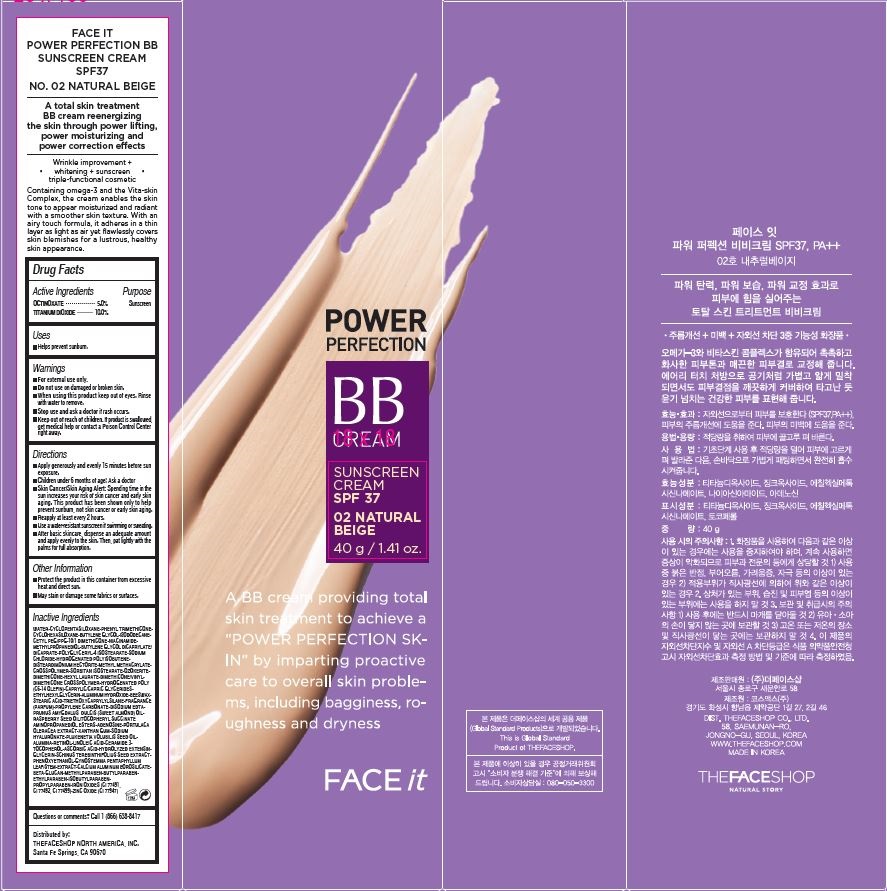 DRUG LABEL: FACE IT POWER PERFECTION
NDC: 51523-312 | Form: CREAM
Manufacturer: THEFACESHOP CO., LTD.
Category: otc | Type: HUMAN OTC DRUG LABEL
Date: 20141120

ACTIVE INGREDIENTS: OCTINOXATE 2 g/40 g; TITANIUM DIOXIDE 4 g/40 g
INACTIVE INGREDIENTS: WATER

Face it Power Perfection 32800312

Active Ingredients

OCTINOXATE • • • • • • • • • • • • 5.0%

TITANIUM DIOXIDE • • • • • • • • 10.0%

Purpose

Sunscreen
Sunscreen

Uses

Helps prevent sunburn.

Warnings

For external use only.

Do not use on damaged or broken skin.

When using this product keep out of eyes.

Rinse with water to remove.

Stop use and ask a doctor if rash occurs.

Keep out of reach of children.

If product is swallowed, get medical help

or contact a Poison Control Center right away.

Directions

Apply generously and evenly 15 minutes before sun

exposure.

Children under 6 months of age: Ask a doctor

Skin Cancer/Skin Aging Alert: Spending time in the

sun increases your risk of skin cancer and early skin

aging. This product has been shown only to help

prevent sunburn, not skin cancer or early skin aging.

Reapply at least every 2 hours.

Use a water-resistant sunscreen if swimming or sweating.

After basic skincare, dispense an adequate amount

and apply evenly to the skin. Then, pat lightly with the

palms for full absorption.

Other Information

Protect the product in this container from excessive

heat and direct sun.

May stain or damage some fabrics or surfaces.

Inactive Ingredients

WATER•CYCLOPENTASILOXANE•PHENYL TRIMETHICONE•

CYCLOHEXASILOXANE•BUTYLENE GLYCOL•ISODODECANE•

CETYL PEG/PPG-10/1 DIMETHICONE•NIACINAMIDE•

METHYLPROPANEDIOL•BUTYLENE GLYCOL DICAPRYLATE/

DICAPRATE•POLYGLYCERYL-4 ISOSTEARATE•SODIUM

CHLORIDE•HYDROGENATED POLYISOBUTENE•

DISTEARDIMONIUM HECTORITE•METHYL METHACRYLATE•

CROSSPOLYMER•SORBITAN ISOSTEARATE•OZOKERITE•

DIMETHICONE•HEXYL LAURATE•DIMETHICONE/VINYL•

DIMETHICONE CROSSPOLYMER•HYDROGENATED POLY

(C6-14 OLEFIN)•CAPRYLIC/CAPRIC GLYCERIDES•

ETHYLHEXYLGLYCERIN•ALUMINUM HYDROXIDE•BEESWAX•

STEARIC ACID•TRIETHOXYCAPRYLYLSILANE•FRAGRANCE

(PARFUM)•PROPYLENE CARBONATE•DISODIUM EDTA•

PRUNUS AMYGDALUS DULCIS (SWEET ALMOND) OIL•

RASPBERRY SEED OIL/TOCOPHERYL SUCCINATE

AMINOPROPANEDIOL ESTERS•ADENOSINE•PORTULACA

OLERACEA EXTRACT•XANTHAN GUM•SODIUM

HYALURONATE•PLUKENETIA VOLUBILIS SEED OIL•

ALUMINA•RETINOL•LINOLEIC ACID•CERAMIDE 3•

TOCOPHEROL•ASCORBIC ACID•HYDROLYZED EXTENSIN•

GLYCERIN•SCHINUS TEREBINTHIFOLIUS SEED EXTRACT•

PHENOXYETHANOL•GYNOSTEMMA PENTAPHYLLUM

LEAF/STEM•EXTRACT•CALCIUM ALUMINUM BOROSILICATE•

BETA-GLUCAN•METHYLPARABEN•BUTYLPARABEN•

ETHYLPARABEN•ISOBUTYLPARABEN•

PROPYLPARABEN•IRON OXIDES (CI 77491,

CI 77492, CI 77499)•ZINC OXIDE (CI 77947)

Questions

Questions or comments? Call 1 (866) 638-8417

Distributed by:

THEFACESHOP NORTH AMERICA, INC.

Santa Fe Springs, CA 90670

PACKAGE LABEL

POWER PERFECTION

BB CREAM

SUNSCREEN CREAM SPF37

02 NATURAL BEIGE

A BB cream providing total skin treatment

to achieve a "POWER PERFECTION SKIN"

by imparting proactive care to overall skin problems,

including bagginess, roughness and dryness.